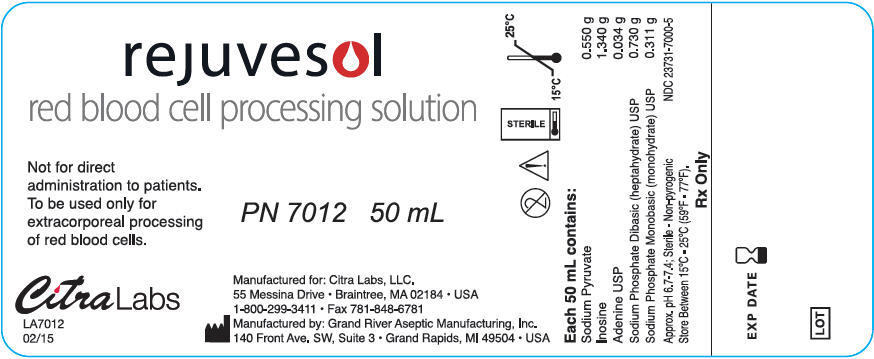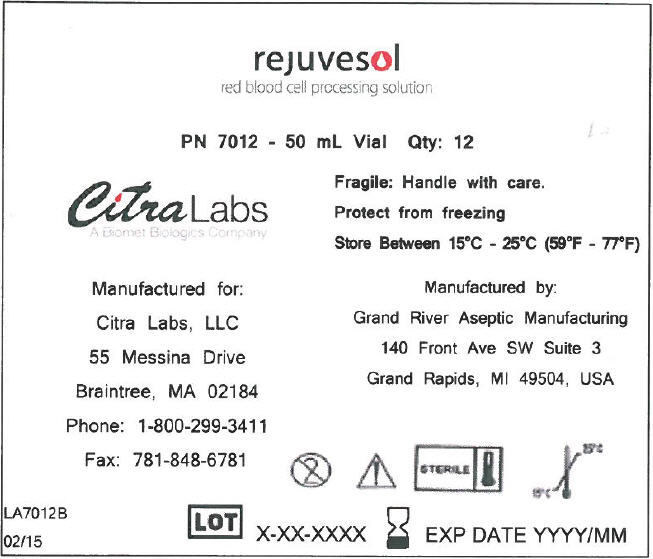 DRUG LABEL: Rejuvesol
NDC: 23731-7000 | Form: SOLUTION
Manufacturer: Citra Labs, LLC
Category: prescription | Type: HUMAN PRESCRIPTION DRUG LABEL
Date: 20230214

ACTIVE INGREDIENTS: SODIUM PYRUVATE 0.55 g/50 mL; INOSINE 1.34 g/50 mL; ADENINE 0.034 g/50 mL; SODIUM PHOSPHATE, DIBASIC 0.73 g/50 mL; SODIUM PHOSPHATE, MONOBASIC, MONOHYDRATE 0.311 g/50 mL

rejuvesol
red blood cell processing solution

For Use in the Extracorporeal Rejuvenation of Red Blood Cells

50 mL Glass Vial
NDC 23731-7000-5
PN 7012 12 Vials/Case

DESCRIPTION

Rejuvesol® Red Blood Cell Processing Solution (rejuvesol® Solution) is a sterile, non-pyrogenic solution of sodium pyruvate, inosine, adenine, dibasic sodium phosphate, and monobasic sodium phosphate in water for injection intended only for use in the extracorporeal rejuvenation of a unit of red blood cell concentrate (RBC). Each 50 mL of rejuvesol® Solution contains sodium pyruvate 0.550 g, inosine 1.34 g, adenine 0.034 g, dibasic sodium phosphate (heptahydrate) 0.730 g, and monobasic sodium phosphate (monohydrate) 0.311 g, in water for injection, pH 6.7-7.4.

CLINICAL PHARMACOLOGY

A gradual depletion of red blood cell adenosine triphosphate (ATP) and 2,3 diphosphoglycerate (2,3-DPG) occurs with storage of RBC at 1-6 °C.^1 The level of 2,3-DPG in RBC stored for greater than 14 days is less than 10% of normal^1,2,12,17,18. Rejuvenation of RBC with rejuvesol® Solution increases the levels of ATP and 2,3-DPG.^(1-5,8,13,17-22,24, 25)

An in vitro loss of red blood cells occurs with the preservation and processing of RBC. Thus, the effectiveness of a transfusion is influenced by both the total number of red blood cells transfused and the number of those cells which remain in circulation. Therefore, the "dose" of a transfusion is defined as the percentage of pre-transfusion recovered red blood cells multiplied by the 24 hour post-transfusion survival value.

Rejuvenation is accomplished by incubating the contents of one 50 mL vial of rejuvesol® Solution with one unit of RBC (prepared from up to 550 mL of whole blood) for sixty (60) minutes at 37 °C. Citra recommends that the entire 50 mL of rejuvesol® Solution be added to a "smaller than normal" RBC as long as the prerejuvenation net packed cell weight is greater than 110 grams.^1,9

INDICATION AND USAGE

Rejuvesol® Solution is intended only to be used as an in vitro processing solution for the rejuvenation of a unit of RBC. RBC may be rejuvenated after storage in CPD (non-leukocyte reduced), CPDA-1, (non-leukocyte reduced), CPD/ADSOL® (CPD/AS-1 leukocyte reduced), or CP2D/Nutricel® (CP2D/AS-3, leukocyte reduced). The final concentration of ATP and 2,3-DPG achieved after rejuvenation will vary depending on the number of days of liquid storage at 1-6 °C prior to rejuvenation. NOTE: For simplicity, RBC stored in CPD (non-leukocyte reduced), CPDA-1 (non-leukocyte reduced), CPD/ADSOL® (CPD/AS-1 leukocyte reduced), CP2D/Nutricel® (CP2D/AS-3, leukocyte reduced) are referred to hereafter as CPD, CPDA-1, CPD/AS-1, and CP2D/AS-3, respectively. Citra Labs, LLC, recommends that rejuvenation of RBC be performed after 14 days or longer of liquid storage. RBC (CPD, CPDA-1, CPD/AS-1, and CP2D/AS-3) rejuvenated before 6 days of storage may achieve 2,3-DPG levels in excess of 2 times normal and ATP levels in excess of 1.5 times normal^5,6 (See Warning and Contraindications).

Rejuvenation of CPD or CPDA-1 RBC for Immediate use or for Cryopreservation

RBC which have been collected and stored in CPD or CPDA-1 anticoagulant may be rejuvenated up to three days after the expiration date of the RBC, as long as storage at 1-6 °C is not interrupted.^3,4 After rejuvenation, RBC (CPD and CPDA-1) must be either washed and stored at 1-6 °C for up to 24 hours prior to transfusion or glycerolized and frozen at –80 °C (below –65 °C). Red Blood Cells Frozen Rejuvenated which were collected and stored in CPD or CPDA-1 may be stored frozen up to 10 years.^10

When RBC are rejuvenated after maximum liquid storage, i.e., CPD RBC at 24 days or CPDA-1 RBC at 38 days, the concentrations of 2,3-DPG and ATP increase typically to above normal.^1,3-5,6

CAUTION: RBC collected in CPD or CPDA-1 cannot be leukocyte reduced prior to rejuvenation.

Rejuvenation of CPD/AS-1 RBC or CP2D/AS-3

Rejuvesol® Solution has not been approved for the rejuvenation of RBC stored in any additive systems other than AS-1 or AS-3. RBC stored in CPD/AS-1 or CP2D/AS-3 at 1-6 °C may be rejuvenated up to, but not exceeding, 42 days of storage as long as storage at 1-6 °C is not interrupted. Rejuvenated CPD/AS-1 RBC must be either washed and stored at 1-6 °C for up to 24 hours prior to transfusion or glycerolized and frozen at –80 °C (below –65 °C). Red Blood Cells Frozen Rejuvenated which were collected and stored in CPD/AS-1 may be stored for up to 3 years. Rejuvenated CP2D/AS-3 RBC must be washed and stored at 1-6 °C for up to 24 hours prior to transfusion. Unlike rejuvenated CPD, CPDA-1, CPD/AS-1 RBC, and CP2D/AS-3, rejuvenated RBC collected and stored in any other anticoagulant/additive solution combination have not been approved to be immediately washed and transfused or for cryopreservation.

Rejuvenation of CPD/AS-1 RBC for Cryopreservation

When CPD/AS-1 RBC are rejuvenated at 42 days of liquid storage, frozen, deglycerolized, and stored for 24 hours, the concentration of 2,3-DPG and ATP increases to above normal. In a limited study, the average 24 hour post-transfusion survival value of these cells was statistically higher than the reported^12 survival value of CPD/AS-1 red blood cell concentrates which are stored for 42 days prior to transfusion. The "dose" may be equivalent for a CPD/AS-1 RBC whether the unit is stored for 42 days prior to transfusion or stored for 42 days, rejuvenated, frozen, deglycerolized, and stored for 24 hours prior to transfusion. Unlike rejuvenated CPD/AS-1 RBC, rejuvenated RBC (CP2D/AS-3) has not been approved for cryopreservation.

Rejuvenation of CPD/AS-1 RBC or CP2D/AS-3 for Immediate Use

When CPD/AS-1 RBC are rejuvenated at 42 days of liquid storage, washed, and stored for 24 hours, the concentration of ATP increases to day 0 values. For 2,3-DPG rejuvenation of RBCs stored in CPD/AS-1 for 42 days, the range of 2,3 DPG relative to day 0 value was 46%-172% with a mean of 98% ± 29%. For 66% of the RBC units (44/67, 33/33 in Site A and 11/34 in Site B) the concentration of 2,3-DPG reached at least 80% of the day 0 value.

When CP2D/AS-3 RBC are rejuvenated at 42 days of liquid storage, washed, and stored for 24 hours, the concentration of ATP increases to day 0 values. For 2,3-DPG rejuvenation of RBCs stored in CPD/AS-1 for 42 days, the range of 2,3 DPG relative to day 0 value was 48%-150% with a mean of 96% ± 23%. For 76% of the RBC units (52/68, 30/35 in Site A and 22/33 in Site B) the concentration of 2,3-DPG reached at least 80% of the day 0 value.

WARNING AND CONTRAINDICATIONS

Rejuvesol® Solution is intended only for the extracorporeal rejuvenation of a RBC. It should never be directly administered to Humans.

Rejuvesol® Solution must not be added to whole blood because the additional plasma may reduce the effectiveness of the rejuvenation process. Immediately after rejuvenation, RBC must either be washed via an approved protocol prior to transfusion or glycerolized and frozen. RBC which have been rejuvenated, glycerolized, and frozen must be deglycerolized via an approved protocol prior to transfusion.

RBC rejuvenated before 6 days of storage may achieve 2,3-DPG levels in excess of 2 times normal and ATP levels in excess of 1.5 times normal.^5,6 In patients with reduced arterial blood p02 of less than 40 torr, the use of RBC rejuvenated before 6 days of storage are contraindicated because their high 2,3-DPG levels and low oxygen affinity may impair proper oxygenation of the red blood cells in the lung.^7

Rejuvenated RBC are further processed prior to transfusion to remove the un-used portion of rejuvesol® Solution, by-products of the rejuvenation process, and any other potential storage-related impurities in rejuvesol® Solution. Based on the concentration of the residual inosine in rejuvenated RBC that are either washed or deglycerolized, the average washout of inosine was calculated to be > 97.4%. A literature search for potential toxicity associated with the ingredients that comprise rejuvesol® Solution, including potential metabolites, was conducted.^23 This report concludes that no theoretical contraindications would be associated with the transfusion of a single unit of unwashed, rejuvenated RBC that would contain amounts of pyruvate, inosine, adenine, phosphate, hypoxanthine, uric acid, and lactate that exceed reference values (excluding lactate) as these substances are naturally metabolized and/or are excreted.^23

The maximum number of properly processed rejuvenated RBC that can be transfused to a single recipient over their entire lifetime has not been determined.

PRECAUTIONS

- Aseptic technique must be maintained at all times.
- Do not use unless solution is clear/colorless and seal is intact. Product that exhibits a slight yellow color should not be used. Product instability has been observed after continuous exposure at high temperature (after 6 months at 40 °C and after 9 months at >30 °C).
- This product contains no bacteriostatic or antimicrobial agents and is intended for single use only.
- Rx Only - Federal (USA) law prohibits dispensing without prescription.

STORAGE

It is recommended that the product be stored at 15 - 25 °C (59 - 77 °F). Protect from freezing. Exposure to temperatures near or below freezing may produce a white precipitate in the solution; this precipitate will dissolve upon brief incubation at room temperature. Alternatively, the product may be warmed at 37 °C for up to one hour in a dry air incubator to dissolve the precipitate.

HOW SUPPLIED

PN 7012: 50 mL vial; 12 vials per case

DIRECTIONS FOR REJUVENATION OF CPD, CPDA-1, CPD/AS-1, OR CP2D/AS-3 RBC PRIOR TO IMMEDIATE USE^3,11,25

NOTE: REJUVENATED RBC STORED IN ANY OTHER ANTICOAGULANT/ADDITIVE SOLUTION COMBINATION HAVE NOT BEEN APPROVED TO BE IMMEDIATELY WASHED AND TRANSFUSED.

MATERIALS AND EQUIPMENT

(As Suggested or Equivalent)

1. An FDA cleared cell washer/washing system.
2. Temperature-controlled (circulating) water bath (Blue-M MW-1140A, Helmer DH-4).
3. Integral tubing sealer (Sebra 1100).
4. Alcohol swabs (70%) (B-D 6894).
5. One vial (50 mL) of rejuvesol® Red Blood Cell Processing Solution, rejuvesol® Solution (Citra PN 7012)
6. Y-type Rejuvenation Set for the addition of rejuvesol® Solution (Citra PN 7212) or equivalent.
7. Two watertight plastic overwrap bags (Kapak, Scotchpack, 404).
8. Waterproof tape (3M R202).
9. Overwrap bag impulse sealer (Stericon 210X).

PROCEDURE

I. TO COMBINE rejuvesol® Solution WITH THE RBC

1. Remove the flip-off protective cap from the rejuvesol® Solution vial and swab the exposed rubber stopper surface with an alcohol swab.
2. Close all slide clamps of the Y-type Rejuvenation Set (Citra PN 7212). Heat seal the integral tubing between the 300 mL transfer bag and the Y connector, detach and discard the empty transfer bag.
3. Aseptically, insert the vented spike of the Y-type Rejuvenation Set into the stopper of the vial of rejuvesol® Solution.
4. Join the tubing of the Y-type Rejuvenation Set to the integral tubing of the primary collection bag using a sterile docking device. Alternately, aseptically insert the bag spike of the Y-type Rejuvenation Set into one of the administration ports of the primary collection bag.
5. Elevate the rejuvesol® Solution vial approximately 28 inches above the primary collection bag.
6. Squeeze the drip chamber to prime the system and open the slide clamp of the Y-type Rejuvenation Set.
7. Allow the entire contents of the rejuvesol® Solution vial to flow into the primary collection bag while gently agitating the mixture. This typically takes between 15 and 30 seconds.
8. After all the rejuvesol® Solution has been transferred, close the slide clamp and heat seal the tubing three times between the portion of the Y-type Rejuvenation Set that connects the rejuvesol® Solution vial to the primary collection bag.
9. Cut the middle heat seal and discard the used tubing and empty rejuvesol® Solution vial.
10. Proceed immediately to Section II.

II. TO INCUBATE THE RED BLOOD CELL/ rejuvesol® Solution MIXTURE FOR 60 MINUTES AT 37 °C^3,11,25

NOTE: The timing of incubation is measured from the time the red blood cell/ rejuvesol® Solution mixture is introduced into the water bath. The actual temperature of the red blood cell/ rejuvesol® Solution mixture does not reach 37 °C (the final temperature is usually 29-31 °C).

1. Place the primary collection bag containing the red blood cell/ rejuvesol® Solution mixture into a plastic overwrap bag and flatten the overwrap bag to remove all air prior to sealing
2. Seal the plastic overwrap bag with tape or heat seal.
3. Place the sealed overwrapped unit inside a second overwrap bag containing lead weights (to keep the unit submerged during incubation); flatten and seal.
4. Place the overwrapped unit in the water bath and secure the overwrapped unit to the inside wall of the water bath with waterproof tape.
5. Incubate the overwrapped unit in a 37 °C water bath for 60 minutes with agitation.
6. Remove the overwrapped bag from the water bath, dry the outer overwrap bag with clean, disposable toweling and carefully remove the plastic overwraps from the red blood cell/ rejuvesol® Solution mixture assuring that the primary collection bag and mixture are not contaminated with any water from the water bath.

III. TO PROCESS THE RED BLOOD CELL/rejuvesol® Solution MIXTURE AFTER INCUBATION^3,11

Remove the excess rejuvesol® Solution after rejuvenation by use of an approved cell washing system and standard operating procedures for that system.^3 The rejuvenated, washed RBC may be stored at 1-6 °C for up to 24 hours prior to transfusion.^3,10,11

NOTES:

- No more than four (4) hours should elapse between the time the unit is removed from the refrigerator and the time the cells are placed in the refrigerator.^11
- Rejuvenated-washed RBC not intended for immediate use should be resuspended in 0.9% Sodium Chloride, 0.2% Dextrose for storage at 1-6 °C. Then, just prior to use, to ensure <1% hemolysis in the final product, concentrate the RBC according to local SOP proven to achieve a hematocrit of approximately 80%.^9,24

DIRECTIONS FOR REJUVENATION OF CPD OR CPDA-1 RBC PRIOR TO CRYOPRESERVATION IN AN 800 ML PRIMARY COLLECTION BAG

NOTE: One 50 mL vial of rejuvesol® Solution can be used to rejuvenate one unit of RBC derived from 450 mL, or the volume as stated in the package insert for the 800 mL primary collection bag, of whole blood when collected in an 800 mL primary collection bag.

MATERIALS AND EQUIPMENT

(As Suggested or Equivalent)

1. Temperature-controlled (circulating) water bath (Blue-M MW-1140A, Helmer DH-4).
2. Integral tubing sealer (Sebra 1100).
3. Alcohol swabs (70%) (B-D 6894).
4. One vial (50 mL) of rejuvesol Red Blood Cell Processing Solution, rejuvesol® Solution (Citra PN 7012).
5. Tubing set for the addition of rejuvesol® Solution and glycerol solution - Rejuvenation Harness 28" (71 cm), MedSep, Corp. Code #980-52 or Y-type transfer set, Baxter International #4C1921 or equivalent.
6. Two watertight plastic overwrap bags (Kapak, Scotchpack, 404).
7. Waterproof tape (3M R202).
8. Overwrap bag impulse sealer (Stericon 210X).
9. Filtered airway needle (BD 5200) (Used only with Baxter International #4C1921).

PROCEDURE

I. TO COMBINE rejuvesol® Solution WITH THE RBC^7

1. Remove the flip-off protective cap from the rejuvesol® Solution vial and swab the exposed rubber stopper surface with an alcohol swab.
2. Close all clamps.
3. Aseptically insert the appropriate spike or needle of the tubing set through the rubber stopper of the vial of rejuvesol® Solution.
4. Aseptically insert the bag spike of the tubing set into the adaptor port on the integral tubing of the primary collection bag.
5. Elevate the rejuvesol® Solution vial 28 inches above the primary collection bag.
6. If a drip chamber is on the tubing set, squeeze the drip chamber to prime the system and open the clamp of the tubing set. If there is no drip chamber on the tubing set, open the clamp and aseptically insert a filtered airway needle through the rubber stopper of the vial of rejuvesol® Solution.
7. Allow the entire contents of the rejuvesol® Solution to flow into the primary collection bag while gently agitating the mixture. This typically takes between 15 and 30 seconds.
8. After all of the rejuvesol® Solution has been transferred, close the clamp and heat seal the tubing three times between the portion of the tubing set that connects the rejuvesol® Solution vial to the Y-connector so that the unused vented spike remains attached to the adaptor port.
9. Cut the middle heat seal and discard the used tubing and empty rejuvesol® Solution vial.
10. Proceed immediately to Section II.

II. TO INCUBATE THE RED BLOOD CELL/rejuvesol® Solution MIXTURE FOR 60 MINUTES AT 37 °C^1,7,10,11

NOTE: The timing of the incubation is measured from the time the red blood cell/ rejuvesol® Solution mixture is introduced into the water bath. The actual temperature of the red blood cell/ rejuvesol® Solution mixture does not reach 37 °C (the final temperature is usually 29-31 °C).

1. Place the primary collection bag containing the red blood cell/ rejuvesol® Solution mixture into a plastic overwrap bag with the unused portion of the Rejuvenation Harness or Y-type Transfer Set and flatten the overwrap to remove all air prior to sealing.
2. Seal the plastic bag with tape or heat seal.
3. Place the sealed overwrapped unit inside a second overwrap bag containing lead weights (to keep the unit submerged during incubation); flatten and seal.
4. Place the overwrapped unit in the water bath. Secure the overwrap bag to the inside wall of the water bath with waterproof tape.
5. Incubate the unit in a 37 °C water bath for 60 minutes.
6. Remove the overwrapped unit from the water bath; dry the outer overwrap bag with clean, disposable toweling and carefully remove the plastic overwraps from the red blood cell/ rejuvesol® Solution mixture assuring that the primary collection bag and mixture are not contaminated with any water from the water bath.

NOTE: Centrifugation after rejuvenation is not required for RBC intended to be frozen in the 800 mL Primary Collection Bag. Glycerolized RBC are centrifuged prior to freezing.

III. TO PROCESS THE RED BLOOD CELL/rejuvesol® Solution MIXTURE AFTER INCUBATION^7

1. After the 60 minute incubation at 37 °C, the red blood cell/ rejuvesol® Solution mixture is ready for immediate glycerolization.
2. Complete the glycerolization per Standard Operating Procedure.^7

NOTES:

- Rejuvenated-glycerolized RBC to be frozen in the 800 mL primary collection bag must be concentrated to achieve a hematocrit of approximately 60 ± 5 % after glycerolization per Standard Operating Procedure.^7
- No more than four (4) hours should elapse between the time the unit is removed from the refrigerator and the time the cells are placed in the freezer.^11
- Rejuvenated-deglycerolized RBC not intended for immediate use should be resuspended in 0.9% Sodium Chloride, 0.2% Dextrose for storage at 1-6 °C. Then, just prior to use, to ensure < 1% hemolysis in the final product, concentrate the RBC following local SOP proven to achieve a hematocrit of approximately 85%.^7,9,24

DIRECTIONS FOR REJUVENATION OF CPD, CPDA-1, OR CPD/AS-1 RBC PRIOR TO CRYOPRESERVATION

NOTE: REJUVENATED RBC STORED IN ANY OTHER ANTICOAGULANT/ADDITIVE SOLUTION COMBINATION HAVE NOT BEEN APPROVED FOR CRYOPRESERVATION.

MATERIALS AND EQUIPMENT

(As Suggested or Equivalent)

1. Temperature-controlled (circulating) water bath (Blue-M MW-1140A, Helmer DH-4).
2. Integral tubing sealer (Sebra 1100)
3. Alcohol swabs (70%) (B-D 6894).
4. One vial (50 mL) of rejuvesol® Red Blood Cell Processing Solution, rejuvesol® Solution (Citra PN 7012).
5. Y-type Rejuvenation Set for the addition of rejuvesol® Solution (Citra PN 7212) or equivalent.
6. Two watertight plastic overwrap bags (Kapak, Scotchpack, 404).
7. Waterproof tape (3M R202).
8. Overwrap bag impulse sealer (Stericon 210X).

PROCEDURE

I. TO COMBINE rejuvesol® Solution WITH THE RBC

1. Remove the flip-off protective cap from the rejuvesol® Solution vial and swab the exposed rubber stopper surface with an alcohol swab.
2. Close all slide clamps of the Y-type Rejuvenation Set (Citra PN 7212).
3. Aseptically, insert the vented spike of the Y-type Rejuvenation Set into the stopper of the vial of rejuvesol® Solution.
4. Join the tubing of the Y-type Rejuvenation Set to the integral tubing of the primary collection bag using a sterile docking device. Alternately, aseptically insert the bag spike of the Y-type Rejuvenation Set into one of the administration ports of the primary collection bag.
5. Elevate the rejuvesol® Solution vial approximately 28 inches above the primary collection bag.
6. Squeeze the drip chamber to prime the system and open the slide clamp of the Y-type Rejuvenation Set.
7. Allow the entire contents of the rejuvesol® Solution vial to flow into the primary bag while gently agitating the mixture. This typically takes between 15 and 30 seconds.
8. After all of the rejuvesol® Solution has been transferred, close the slide clamp and heat seal the tubing three times between the portion of the Y-type Rejuvenation Set that connects the rejuvesol® Solution vial to the primary collection bag.
9. Cut the middle heat seal and discard the used tubing and empty rejuvesol® Solution vial.
10. Proceed immediately to Section II.

II. TO INCUBATE THE RED BLOOD CELL/rejuvesol® Solution MIXTURE FOR 60 MINUTES AT 37 °C^1,8,9,11,13

NOTE: The timing of the incubation is measured from the time the red blood cell/ rejuvesol® Solution mixture is introduced into the water bath. The actual temperature of the red blood cell/ rejuvesol® Solution mixture does not reach 37 °C (the final temperature is usually 29-31 °C).

1. Place the primary collection bag containing the red blood cell/ rejuvesol® Solution mixture with the attached transfer bag of the Y-type Rejuvenation Set in a plastic overwrap bag and flatten the overwrap to remove all air prior to sealing.
2. Seal the plastic overwrap with tape or heat seal.
3. Place the sealed overwrapped unit inside a second overwrap bag containing lead weights (to keep the unit submerged during incubation); flatten and seal.
4. Place the overwrapped unit in the water bath and secure the overwrap to the inside wall of the water bath with waterproof tape.
5. Incubate the unit in a 37 °C water bath for 60 minutes with agitation.
6. Remove the overwrapped unit from the water bath; dry the outer overwrap with clean, disposable toweling and carefully remove the overwraps from the red blood cell/ rejuvesol® Solution mixture assuring that the primary collection bag and mixture are not contaminated with any water from the water bath.

III. TO PROCESS THE RED BLOOD CELL/rejuvesol® Solution MIXTURE AFTER INCUBATION^1,9,11,13

Complete the glycerolization procedure per Standard Operating Procedure.^1,10,11

NOTES:

- After incubation, the red blood cell/ rejuvesol® Solution mixture may need to be concentrated prior to the addition of glycerol solution to insure proper glycerolization.^1,9,11,13
- No more than four (4) hours should elapse between the time the unit is removed from the refrigerator and the time the cells are placed in the freezer.^11

REFERENCES

1. Valeri CR, CG Zaroulis, Rejuvenation and Freezing of Outdated Stored Human Red Blood Cells; NEJMED 1972;287:1307-1313.
2. Valeri CR. Unpublished Data.
3. Valeri CR, AD Gray, GP Cassidy, et al.; The 24-hour posttransfusion survival, oxygen transport function, and residual hemolysis of human outdated-rejuvenated red cell concentrates after washing and storage at 4 °C for 24 to 72 hours. Transfusion 1984; 24:323-6.
4. Valeri CR, CG Zaroulis, JJ Vecchione, et al.; Therapeutic effectiveness and safety of outdated human red blood cells rejuvenated to restore oxygen transport function to normal, frozen for 3 to 4 years at –80 °C, washed, and stored at 4 °C for 24 hours prior to rapid infusion. Transfusion 1980; 20:159-70.
5. Valeri, CR, DA Valeri, JJ Vecchione, and CP Emerson; Biochemical modification and freeze preservation of red blood cells, Critical Care Med. 7 (9):439-477, 1979.
6. Valeri CR; Status report on rejuvenation and freezing of red blood cells. Plasma Therapy 2 (3): 155-170, 1981.
7. Boston University School of Medicine/Naval Blood Research Laboratory, Boston, MA Standard Operating Procedure—Red Blood Cells Collected in the CPDA-1 800 mL Primary PVC Plastic Collection Bag System and Stored for 3 to 35 Days (Indated-Rejuvenated) or for 36 to 38 Days (Outdated-Rejuvenated), Biochemically Modified with PIPA Solution Prior to Glycerolization in the Primary 800 mL Bag with the Special Adaptor Port Using 40% W/V Glycerol and Storage at –80 °C, Washed in the Haemonetics Blood Processor 115, and Stored at 4 °C for 24 Hours Prior to Transfusion (Revised 5/91).
8. Whitely, PH, et al; Improved recovery of ATP and 2,3-DPG with agitation during incubation at 37 °C in rejuvesol® Solution treated CPD/AS-1 RBC. Transfusion 53 (supp), SP81, 2013.
9. Valeri CR; Simplification of the Methods for Adding and Removing Glycerol During Freeze-Preservation of Human Red Blood Cells with the High or Low Glycerol Methods: Biochemical Modification Prior to Freezing . Transfusion 15(3): 195-218, 1975.
10. AABB Standards for Blood Banks and Transfusion Services, 27th Edition.
11. American Association of Blood Banks Technical Manual, pages 946-953, 17th Edition, 2011.
12. Valeri CR, LE Pivacek, M Palter, RC Dennis, N Yeston, CP Emerson, and MD Altschule; A clinical experience with ADSOL® preserved erythrocytes. Surgery, Gynecology, and Obstetrics 166:33-46, 1988.
13. Szymanski IO, Teno RA, Lockwood WB, Hudgens, R, and Johnson, GS; Effect of rejuvenation and frozen storage on 42-day-old AS-1 RBCs. Transfusion 41: 550-555, 2001.
14. Gelderman MP and Vostal JG; Rejuvenation Improves Roller Pump-Induces Stress resistance of Fresh and Stored Red Blood Cells. Transfusion 51:1096-1104, 2011.
15. Meyer EK, et al; Rejuvenation Capacity of Red Blood Cells in Additive Solutions Over Long-Term Storage. Transfusion, 51(7):1574-1579, 2011.
16. Koshkaryev A, et al; Rejuvenation Treatment of Stored Red Blood Cells Reverses Storage-Induced Adhesion to Vascular Endothelial Cells. Transfusion, 49:2136-2143, 2009.
17. Dennis RC, et al; Transfusion of 2,3-DPG-Enriched Red Blood Cells to Improve Cardiac Function. Ann. Thor. Surg., 26:16-17, 1978.
18. Valeri CR, et al; Improved Oxygen Delivery to the Myocardium During Hypothermia by Perfusion with 2,3-DPG Enriched Red Blood Cells. Ann. Thorac. Surg., 30(6): 527-535, 1980.
19. Valeri CR, et al; Human Red Blood Cells with Normal or Improved Oxygen Transport Function Prepared and Frozen in the Primary Polyvinyl Chloride Plastic Blood Collection Container. Transfusion and Immunohaematology, 22:467-486, 1979.
20. Ragno G and Valeri, CR, Salvaging of Liquid-Preserved O-Positive and O-Negative Red Blood Cells by Rejuvenation and Freezing. Transfus. Apher. Sci., 35(2): 137-143, 2006.
21. Valeri CR, et al; Automation of the Glycerolization of Red Blood Cells with the High-Separation Bowl in the Haemonetics ACP 215 Instrument. Transfusion 45: 1621-1627, 2005
22. Lockwood WB, et al; Effects of Rejuvenation and Frozen Storage on 42-Day-Old AS-3 RBCs. Transfusion 43(11): 1527-153, 2003.
23. Loeb, WF, V.M.D, Ph.D; A Literature Review to Investigate the Feasibility of Modifying the Current Protocol for Use and Developing New Applications. unpublished communication, 19 Oct 2000.
24. Valeri CR, et al; The Survival, Function, and Hemolysis of Human RBCs Stored at 4 °C in Additive Solution (AS-1, AS-3, and AS-5) for 42 Days and then Biochemically Modified, Frozen, Thawed, Washed, and Stored at 4 °C in Sodium Chloride and Glucose for 24 Hours. Transfusion 40: 1341-1345, 2000.
25. Whitely, PH, et al; Improved ATP and 2,3-DPG recovery using the Sahara III dry-air blood warmer in CPD/AS-1 RBC treated with rejuvesol® Solution. Transfusion 54 (supp), SP69, 2014.
26. Whitely PH, et al; Restoration of morphology following rejuvenation of stored red blood cells (RBC), Transfusion 55 (supp 3), 74A-75A, 2015.
27. Gray AD, et al; Extended Storage (>24 Hours) of Rejuvenated and Washed RBC, Transfusion 55 (supp 3), 68A-69A, 2015.

Rejuvesol® Solution is a registered trademark of Citra Labs, LLC, A Biomet Inc. Company.

ADSOL® is a registered trademark of Fenwal, Inc.

Nutricel® is a registered trademark of Haemonetics, Corp

Manufactured for: Citra Labs, LLC
55 Messina Drive, Braintree, MA 02184 ● USA
1-800-299-3411 ● Fax 781-848-6781
Manufactured by: Grand River Aseptic Manufacturing, Inc.
140 Front Ave SW, Suite 3 Grand Rapids, MI 49504 USA

©2013 CitraLabs
12/15

FL7000
Printed in USA

PRINCIPAL DISPLAY PANEL - 50 mL Vial Label

rejuvesol
red blood cell processing solution

STERILE
15°C - 25°C

Not for direct
administration to patients.
To be used only for
extracorporeal processing
of red blood cells.

PN 7012 50 mL

CitraLabs
A Biomet Inc. Company.

LA7012
02/15

Manufactured for: Citra Labs, LLC.
55 Messina Drive ● Braintree, MA 02184 ● USA
1-800-299-3411 ● Fax 781-848-6781
Manufactured by: Grand River Aseptic Manufacturing, Inc.
140 Front Ave. SW, Suite 3 ● Grand Rapids, MI 49504 ● USA

PRINCIPAL DISPLAY PANEL - 50 mL Vial Case Label

rejuvesol
red blood cell processing solution

PN 7012 - 50 mL Vial Qty: 12

CitraLabs
A Biomet Inc. Company.

Fragile: Handle with care.
Protect from freezing
Store Between 15°C - 25°C (59°F - 77°F)

Manufactured for:
Citra Labs, LLC
55 Messina Drive
Braintree, MA 02184
Phone: 1-800-299-3411
Fax: 781-848-6781

Manufactured by:
Grand River Aseptic Manufacturing, Inc.
140 Front Ave SW Suite 3
Grand Rapids, MI 49504, USA

STERILE
15°C - 25°C

LA7012B
02/15

LOT X-XX-XXXX
EXP DATE YYYY/MM